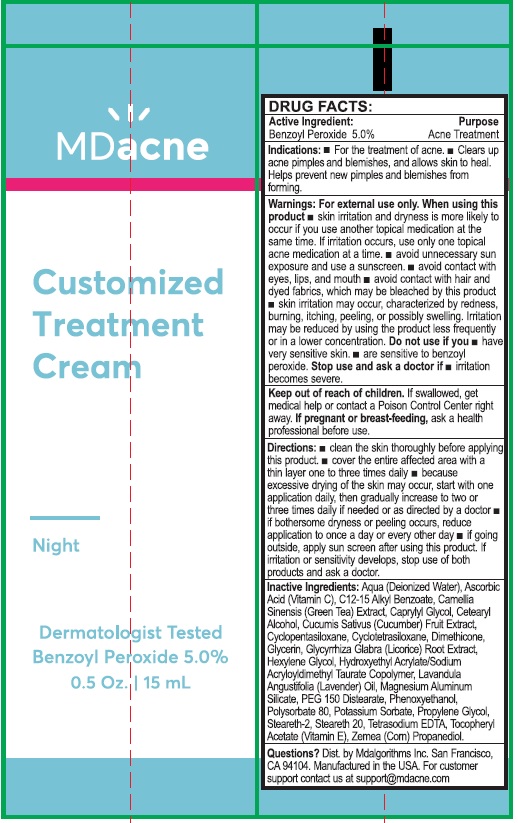 DRUG LABEL: MDacne Customized Cream (Benzoyl Peroxide)
NDC: 71804-250 | Form: CREAM
Manufacturer: MDalgorithms Inc.
Category: otc | Type: HUMAN OTC DRUG LABEL
Date: 20220209

ACTIVE INGREDIENTS: BENZOYL PEROXIDE 5 mg/100 mL
INACTIVE INGREDIENTS: WATER; ASCORBIC ACID; ALKYL (C12-15) BENZOATE; CAMELLIA SINENSIS FLOWER; CAPRYLYL GLYCOL; CETOSTEARYL ALCOHOL; CUCUMBER; CYCLOMETHICONE 5; CYCLOMETHICONE 4; DIMETHICONE; GLYCERIN; GLYCYRRHIZA GLABRA; HEXYLENE GLYCOL; HYDROXYETHYL ACRYLATE/SODIUM ACRYLOYLDIMETHYL TAURATE COPOLYMER (100000 MPA.S AT 1.5%); LAVENDER OIL; MAGNESIUM ALUMINUM SILICATE; PEG-150 DISTEARATE; PHENOXYETHANOL; POLYSORBATE 80; POTASSIUM SORBATE; PROPYLENE GLYCOL; STEARETH-2; STEARETH-20; EDETATE SODIUM; .ALPHA.-TOCOPHEROL; CORN

DRUG FACTS:

Active Ingredient:

Benzoyl Peroxide 5.0%

Purpose

Acne Treatment

Indications: ■ For the treatment of Acne. ■

Clears up acne pimples and blemishes, and

allows skin to heal. Helps prevent new

pimples and blemishes from forming.

Warnings For external use only. When using this
product ■ skin irritation and dryness is more likely to
occur if you use another topical acne medication at the
same time. If irritation occurs, only use one topical
acne medication at one time. ■ avoid unnecessary sun
exposure and use a sunscreen ■ avoid contact with
eyes, lips and mouth ■ avoid contact with hair and
dyed fabrics, which may be bleached by this product.
■ skin irritation may occur, characterized by redness,
burning, itching, peeling, or possibly swelling. Irritation
may be reduced by using the product less frequently
or in a lower concentration. Do not use if you ■ have
very sensitive skin. ■ are sensitive to benzoyl
peroxide. Stop use and ask a doctor if ■ irritation
becomes severe.

KEEP OUT OF REACH OF CHILDREN

Keep out of the reach of children. If swallowed,
get medical help or contact a Poison Control Center right away.

If pregnant or breast feeding, ask

a health professional before use.

DOSAGE AND ADMINISTRATION

Directions: ■ clean the skin thoroughly before applying
this product. ■ cover the entire affected area with a
thin layer one to three times daily ■ because
excessive drying of the skin may occur, start with one
application daily, then gradually increase to two or
three times daily if needed or directed by a doctor. ■
if bothersome dryness or peeling occurs reduce
application to once a day or every other day ■ if going
outside, apply sunscreen after using this product. If
irritation or sensitivity develops, stop use of both
products and ask a doctor.

INACTIVE INGREDIENT

Other Ingredients: Aqua (Deionized Water), Ascorbic
Acid (Vitamin C), C12-15 Alkyl Benzoate, Camellia
Sinensis (Green Tea) Extract, Caprylyl Glycol, Cetearyl
Alcohol, Cucumis Sativus (Cucumber) Fruit Extract,
Cyclopentasiloxane, Cyclotetrasiloxane, Dimethicone,
Glycerin, Glycyrrhiza Glabra (Licorice) Root Extract,
Hexylene Glycol, Hydroxyethyl Acrylate/Sodium
Acryloyldimethyl Taurate Copolymer, Lavandula
Angustifolia (Lavender Oil), Magnesium Aluminum
Silicate, PEG-150 Distearate, Phenoxyethanol,
Polysorbate-80, Potassium Sorbate, Propylene Glycol,
Steareth-2, Steareth-20, Tetrasodium EDTA, Tocopherol
Acetate (Vitamin E), Zemea (Corn) Propanediol.

Questions? Dist. by Mdalgorithms Inc. San Francisco,

CA 94104. Manufactured in the USA. For customer

support contact us at support@mdacne.com

Package Label

MDacne

Customized

Treatment

Cream

Night

Dermatologist Tested

Benzoyl Peroxide 5.0%

0.5 Oz. | 15 mL

res